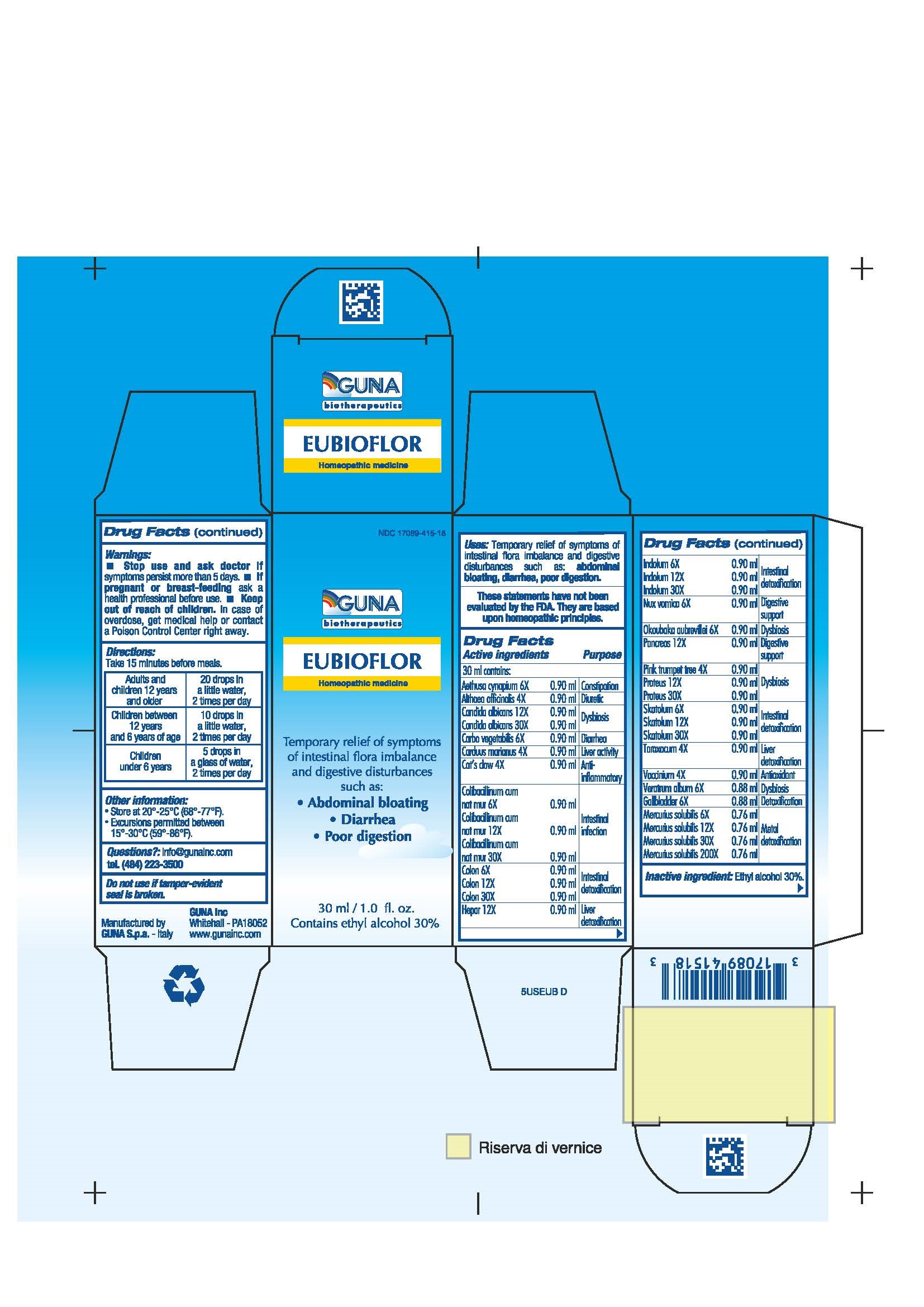 DRUG LABEL: EUBIOFLOR
NDC: 17089-415 | Form: SOLUTION/ DROPS
Manufacturer: Guna spa
Category: homeopathic | Type: HUMAN OTC DRUG LABEL
Date: 20221115

ACTIVE INGREDIENTS: OKOUBAKA AUBREVILLEI BARK 6 [hp_X]/30 mL; SUS SCROFA PANCREAS 12 [hp_X]/30 mL; TABEBUIA IMPETIGINOSA BARK 4 [hp_X]/30 mL; PROTEUS VULGARIS 12 [hp_X]/30 mL; SKATOLE 30 [hp_X]/30 mL; TARAXACUM OFFICINALE 4 [hp_X]/30 mL; BILBERRY 4 [hp_X]/30 mL; VERATRUM ALBUM ROOT 6 [hp_X]/30 mL; MERCURIUS SOLUBILIS 200 [hp_X]/30 mL; AETHUSA CYNAPIUM 6 [hp_X]/30 mL; ALTHAEA OFFICINALIS LEAF 4 [hp_X]/30 mL; CANDIDA ALBICANS 30 [hp_X]/30 mL; ACTIVATED CHARCOAL 6 [hp_X]/30 mL; SILYBUM MARIANUM SEED 4 [hp_X]/30 mL; CAT'S CLAW 4 [hp_X]/30 mL; ESCHERICHIA COLI 30 [hp_X]/30 mL; SUS SCROFA COLON 30 [hp_X]/30 mL; SUS SCROFA GALLBLADDER 6 [hp_X]/30 mL; PORK LIVER 12 [hp_X]/30 mL; INDOLE 12 [hp_X]/30 mL; STRYCHNOS NUX-VOMICA SEED 6 [hp_X]/30 mL
INACTIVE INGREDIENTS: ALCOHOL 9 mL/30 mL

EUBIOFLOR

ACTIVE INGREDIENTS/PURPOSE

- AETHUSA CYNAPIUM 6X CONSTIPATION
- ALTHAEA OFFICINALIS 4X DIURETIC
- CANDIDA ALBICANS 12X,30X DYSBIOSIS
- CARBO VEGETALIS 6X DIARRHEA
- CARDUUS MARIANUS 4X LIVER ACTIVITY
- CAT'S CLAW 4X ANTI-INFLAMMATORY
- COLIBACILLINUM CUM NATRUM MURIATICUM 6X,12X, 30X INTESTINAL INFECTION
- COLON 6X,12X, 30X INTESTINAL DETOXIFICATION
- GALLBLADDER 6X DETOXIFICATION
- HEPAR 12X LIVER DETOXIFICATION
- INDOLUM 6X,12X, 30X INTESTINAL DETOXIFICATION
- MERCURIUS SOLUBILIS 6X,12X, 30X, 200X METAL DETOXIFICATION
- NUX VOMICA 6X DIGESTIVE SUPPORT
- OKOUBAKA AUBREVILLEI 6X DYSBIOSIS
- PANCREAS 12X DIGESTIVE SUPPORT
- PINK TRUMPET TREE 4X DYSBIOSIS
- PROTEUS 12X, 30X DYSBIOSIS
- SKATOLUM 6X,12X,30X INTESTINAL DETOXIFICATION
- TARAXACUM 4X LIVER DETOXIFICATION
- VACCINIUM 4X ANTIOXIDANT
- VERATRUM ALBUM 6X DYSBIOSIS

USES

Temporary relief of symptoms of intestinal flora imbalance and digestive disturbances such as:

- Abdominal bloating
- Diarrhea
- Poor digestion

WARNINGS

- Stop use and ask doctor if symptoms persist more than 5 days.
- If pregnant or breast-feeding ask a health professional before use.
- Keep out of reach of children. In case of overdose, get medical help or contact a Poison Control Center right away.
- Contains ethyl alcohol 30%

PREGNANCY

If pregnant or breast-feeding ask a doctor before use

WARNINGS

Keep this and all medicines out of reach of children

DIRECTIONS

Adults and children 12 years and older 20 drops in a little water, 2 times per day
Children between 12 years and 6 years of age 10 drops in a little water, 2 times per day
Children under 6 years 5 drops in a glass of water, 2 times per day

QUESTIONS

Questions?: info@gunainc.com, tel. (484) 223-3500

INDICATIONS AND USAGE

Take 15 minutes before meals

Inactive ingredient: ethyl alcohol 30%.

keep out of reach of children.